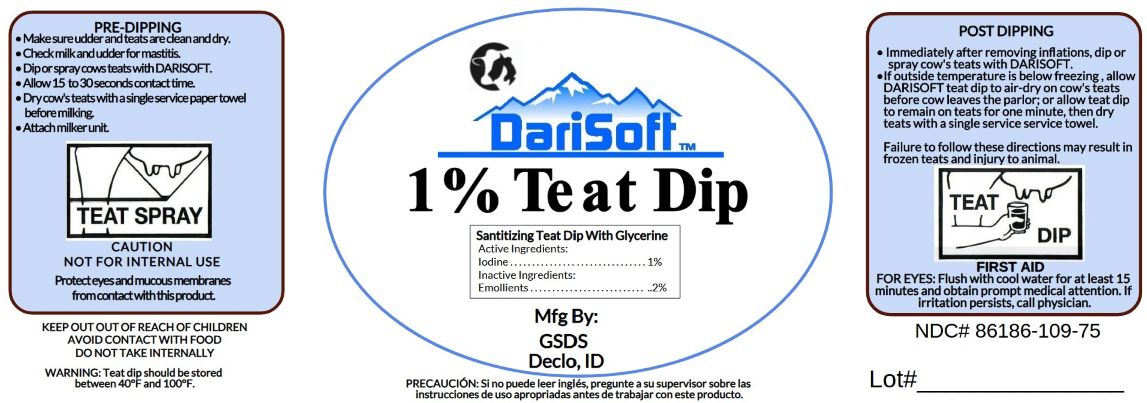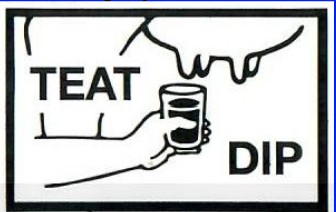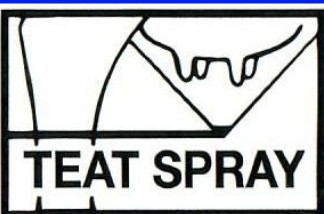 DRUG LABEL: DariSoft 1.0% Teat Dip
NDC: 86186-109 | Form: SOLUTION
Manufacturer: Gem State Dairy Supply
Category: animal | Type: OTC ANIMAL DRUG LABEL
Date: 20250630

ACTIVE INGREDIENTS: IODINE 10 g/1 L
INACTIVE INGREDIENTS: SURFACTIN; GLYCERIN; SODIUM HYDROXIDE; WATER

DariSoft™
1.0% Teat Dip

Active Ingredients:

Iodine............................1.0%

PURPOSE

Sanitizing Teat Dip With Glycerine

INDICATIONS AND USAGE

PRE-DIPPING

- Make sure udder and teats are clean and dry.
- Check milk and udder for mastitis.
- Dip or spray cows teats with DARISOFT.
- Allow 15 to 30 seconds contact time.
- Dry cow's teats with a single service paper towel before milking.
- Attach milker unit.

POST DIPPING

- Immediately after removing inflations, dip or spray cow's teats with DARISOFT.
- If outside temperature is below freezing, allow DARISOFT teat dip to air-dry on cow's teats before cow leaves the parlor; or allow teat dip to remain on teats for one minute, then dry teats with a single service towel.

Failure to follow these directions may result in frozen teats and injury to animal.

PRECAUTIONS

CAUTION

NOT FOR INTERNAL USE

Protect eyes and mucous membranes from contact with this product.

FIRST AID

FOR EYES: Flush with cool water for at least 15 minutes and obtain prompt medical attention. If irritation persists, call physician.

WARNINGS

WARNING: Teat dip should be stored between 40°F and 100°F.

KEEP OUT OF REACH OF CHILDREN

AVOID CONTACT WITH FOOD

DO NOT TAKE INTERNALLY

Inactive ingredients:

Emollients.........................2%

PACKAGE LABEL

Mfg By: GSDS, Delco, ID